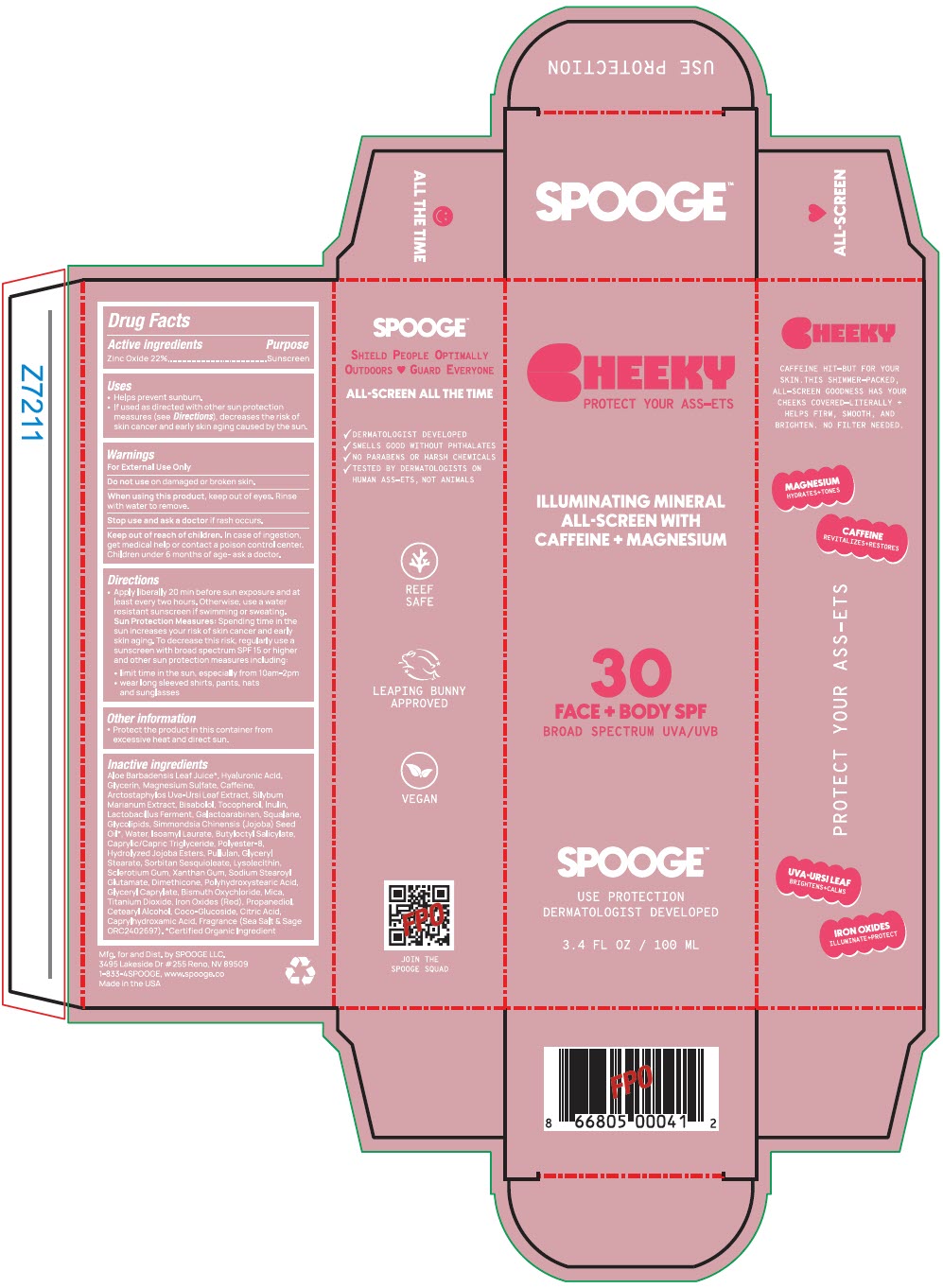 DRUG LABEL: Cheeky
NDC: 85385-357 | Form: LOTION
Manufacturer: Spooge
Category: otc | Type: HUMAN OTC DRUG LABEL
Date: 20250626

ACTIVE INGREDIENTS: Zinc Oxide 22 g/100 mL
INACTIVE INGREDIENTS: ALOE VERA LEAF; HYALURONIC ACID; GLYCERIN; MAGNESIUM SULFATE, UNSPECIFIED FORM; CAFFEINE; ARCTOSTAPHYLOS UVA-URSI LEAF; MILK THISTLE; LEVOMENOL; TOCOPHEROL; INULIN; GALACTOARABINAN; SQUALENE; JOJOBA OIL; WATER; ISOAMYL LAURATE; BUTYLOCTYL SALICYLATE; MEDIUM-CHAIN TRIGLYCERIDES; HYDROLYZED JOJOBA ESTERS (ACID FORM); PULLULAN; GLYCERYL MONOSTEARATE; SORBITAN SESQUIOLEATE; BETASIZOFIRAN; XANTHAN GUM; SODIUM STEAROYL GLUTAMATE; DIMETHICONE, UNSPECIFIED; GLYCERYL MONOCAPRYLATE; BISMUTH OXYCHLORIDE; MICA; TITANIUM DIOXIDE; FERRIC OXIDE RED; PROPANEDIOL; CETOSTEARYL ALCOHOL; COCO-GLUCOSIDE; CITRIC ACID MONOHYDRATE; CAPRYLHYDROXAMIC ACID

Cheeky

Drug Facts

Active ingredients

Zinc Oxide 22%

Purpose

Sunscreen

Uses

- Helps prevent sunburn.
- If used as directed with other sun protection measures (see Directions), decreases the risk of skin cancer and early skin aging caused by the sun

Warnings

For External Use Only

Do not use on damaged or broken skin.

When using this product, keep out of eyes. Rinse with water to remove.

Stop use and ask a doctor if rash occurs.

Keep out of reach of children. In case of ingestion, get medical help or contact a poison control center. Children under 6 months of age- ask a doctor.

Directions

- Apply liberally 20 min before sun exposure and at least every two hours. Otherwise, use a water resistant sunscreen if swimming or sweating.
  Sun Protection Measures: Spending time in the sun increases your risk of skin cancer and early skin aging. To decrease this risk, regularly use a sunscreen with broad spectrum SPF 15 or higher and other sun protection measures including:
  - limit time in the sun, especially from 10am-2pm
  - wear long sleeved shirts, pants, hats and sunglasses

Other information

- Protect the product In this container from excessive heat and direct sun.

INACTIVE INGREDIENTS

Aloe Barbadensis Leaf Juice QSAD, Butyloctyl Salicylate 8%, Caprylic/Capric Triglyceride 6%, Polyester-8 4%, Bismuth Oxychloride 3%, Mica (and) Titanium Dioxide (and) Iron Oxides 3%, Cetearyl Alcohol (and) Coco-Glucoside 2%, Hydrolyzed Jojoba Esters (and) Water 2%, Dimethicone 2%, Glycerin 2%, Fragrance (Sea Salt & Sage ORC2402697) 1.75%, Glyceryl Stearate 1.25%, Iron Oxides (Red) (and) Galactoarabinan 1.25%, Glycolipids 1%, Isoamyl Laurate 1%, Glycerin (and) Water (and) Propanediol (and) Silybum Marianum Extract (and) Arctostaphylos Uva-Ursi Leaf Extract 1%, Squalane 1%, Sorbitan Sesquioleate 1%, Caprylhydroxamic acid (and) Glyceryl Caprylate (and) Glycerin 1%, Polyhydroxystearic Acid 0.6%, Simmondsia Chinensis (Jojoba) Seed Oil 0.5%, Lysolecithin (and) Sclerotium Gum (and) Xanthan Gum (and) Pullulan 0.5%, Sodium Stearoyl Glutamate 0.4%, Bisabolol 0.3%, Tocopherol 0.3%, Citric Acid 0.275%, Inulin 0.1%, Lactobacillus Ferment 0.1%, Magnesium Sulfate 0.1%, Caffeine 0.05%, Sodium Hyaluronate 0.01%, Certified Organic Ingredient

Dist. by SPOOGE LLC.
3495 Lakeside Dr #255 Reno, NV 89509

PRINCIPAL DISPLAY PANEL - 100 ML Tube Box

CHEEKY
PROTECT YOUR ASS-ETS

ILLUMINATING MINERAL
ALL-SCREEN WITH
CAFFEINE + MAGNESIUM

30
FACE + BODY SPF
BROAD SPECTRUM UVA/UVB

SPOOGE™

USE PROTECTION
DERMATOLOGIST DEVELOPED

3.4 FL OZ / 100 ML